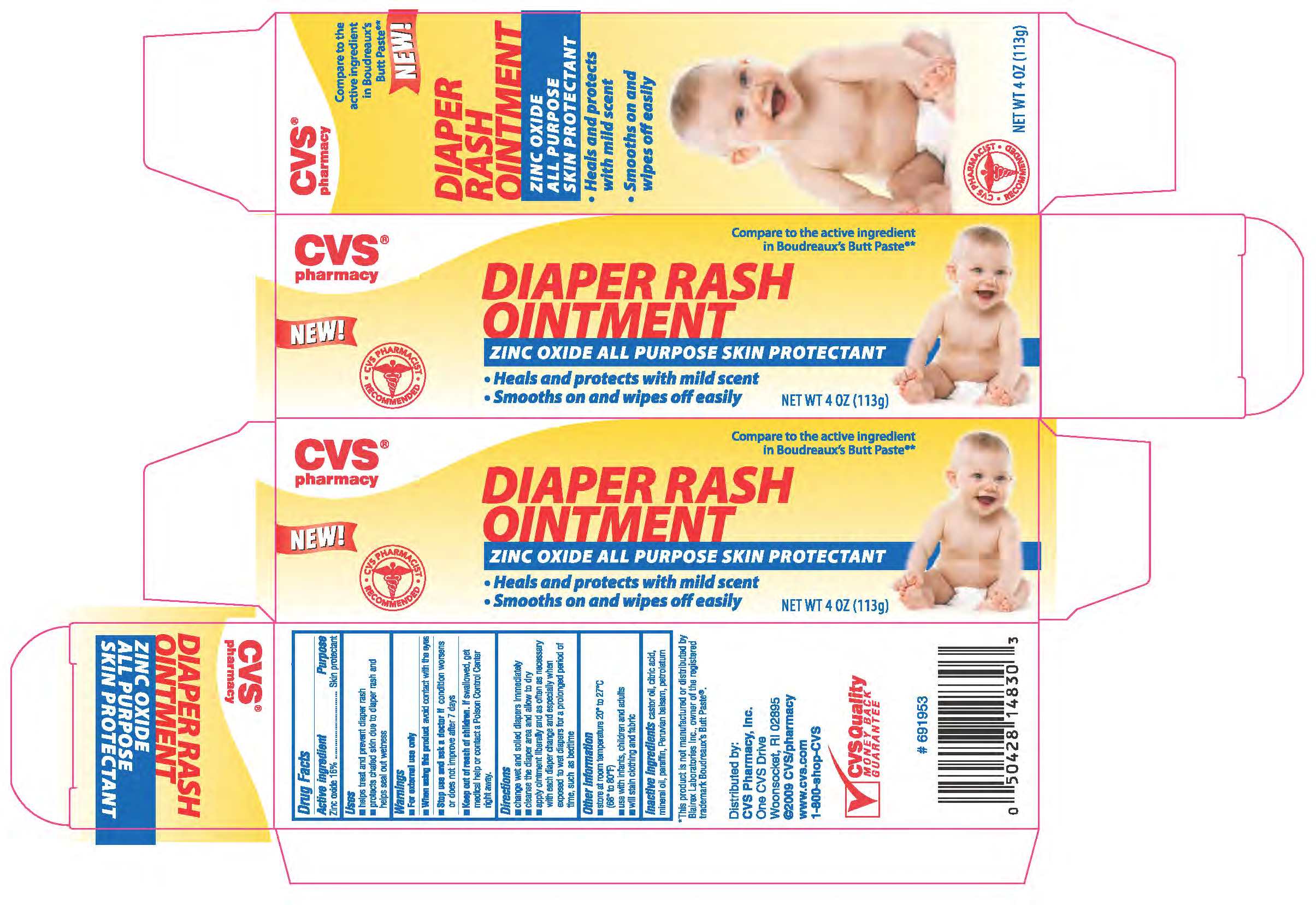 DRUG LABEL: ZINC OXIDE
NDC: 59779-083 | Form: OINTMENT
Manufacturer: CVS
Category: otc | Type: HUMAN OTC DRUG LABEL
Date: 20110216

ACTIVE INGREDIENTS: ZINC OXIDE 160 mg/1 g
INACTIVE INGREDIENTS: PARAFFIN ; MINERAL OIL; ANHYDROUS CITRIC ACID; CASTOR OIL; BALSAM PERU; PETROLATUM

drug facts

Active ingredient Purpose
Zinc oxide 18%.........................Skin protectant

Uses
- helps treat and prevent diaper rash
- protects chafed skin due to diaper rash and
helps seal out wetness

Keep out of reach of children. If swallowed, get
medical help or contact a Poison Control Center right away.

Uses
- helps prevent and treat diaper rash
- protects chafed skin due to diaper rash and
helps seal out wetness

Warnings
For external use only.
_______________________________
When using this product avoid contact with the eyes
_______________________________
Stop use and ask a doctor if condition worsens
or does not improve after seven days
Keep out of reach of children. If swallowed get
medical help or contact a Poison Control Center
right away.

Directions
- change wet and soiled diapers immediately
- cleanse the diaper area and allow to dry
- apply ointment liberally and as often as necessary
with each diaper change and especially when
exposed to wet diapers for a prolonged period of
time such as bedtime.
_______________________________
Other information
- Store at 20 degrees to 25 degrees C (68 degrees to 77 degrees F)
- use with infants children and adults
- will stain clothing and fabric

Inactive Ingredients castor oil, citric acid,
mineral oil, paraffin, Peruvian balsam, petrolatum